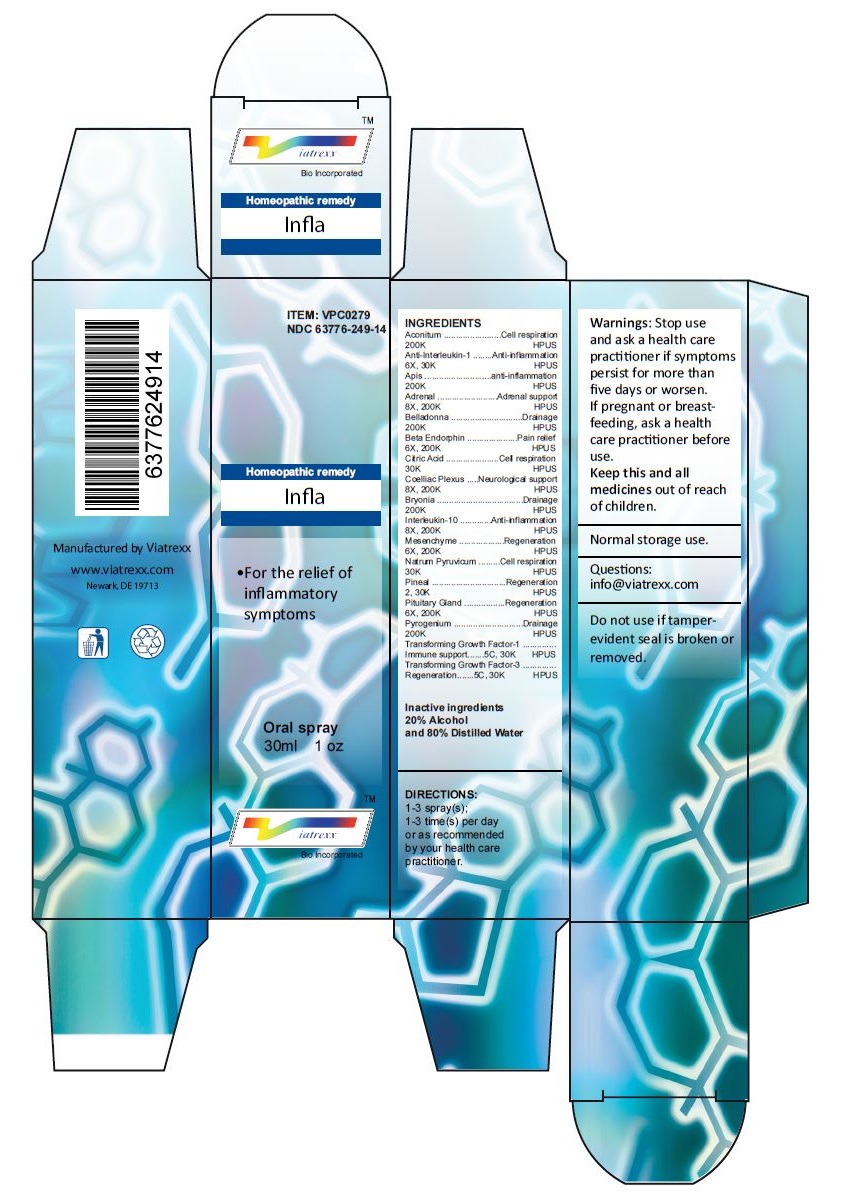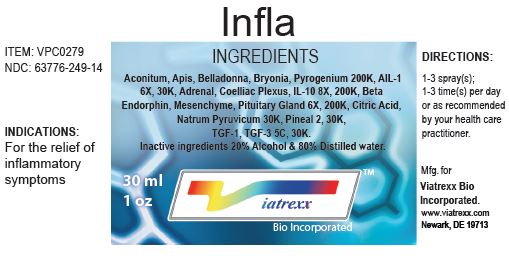 DRUG LABEL: Infla
NDC: 63776-249 | Form: SPRAY
Manufacturer: VIATREXX BIO INCORPORATED
Category: homeopathic | Type: HUMAN OTC DRUG LABEL
Date: 20221130

ACTIVE INGREDIENTS: BRYONIA ALBA ROOT 200 [kp_C]/1 mL; INTERLEUKIN-10 200 [kp_C]/1 mL; BOS TAURUS MESENCHYME 200 [kp_C]/1 mL; SUS SCROFA MESENCHYME 200 [kp_C]/1 mL; SODIUM PYRUVATE 30 [kp_C]/1 mL; BOS TAURUS PINEAL GLAND 30 [kp_C]/1 mL; SUS SCROFA PINEAL GLAND 30 [kp_C]/1 mL; BOS TAURUS PITUITARY GLAND 200 [kp_C]/1 mL; SUS SCROFA PITUITARY GLAND 200 [kp_C]/1 mL; RANCID BEEF 200 [kp_C]/1 mL; TRANSFORMING GROWTH FACTOR BETA-1 30 [kp_C]/1 mL; AVOTERMIN 30 [kp_C]/1 mL; ACONITUM NAPELLUS 200 [kp_C]/1 mL; ANTI-INTERLEUKIN-1.ALPHA. IMMUNOGLOBULIN G RABBIT 30 [kp_C]/1 mL; APIS MELLIFERA 200 [kp_C]/1 mL; BOS TAURUS ADRENAL GLAND 200 [kp_C]/1 mL; SUS SCROFA ADRENAL GLAND 200 [kp_C]/1 mL; ATROPA BELLADONNA 200 [kp_C]/1 mL; METENKEFALIN 200 [kp_C]/1 mL; CITRIC ACID MONOHYDRATE 30 [kp_C]/1 mL; BOS TAURUS SOLAR PLEXUS 200 [kp_C]/1 mL; SUS SCROFA SOLAR PLEXUS 200 [kp_C]/1 mL
INACTIVE INGREDIENTS: ALCOHOL; WATER

Infla

Active Ingredients

Aconitum (200K), Anti-Interleukin-1 (6X, 30K), Apis (200K), Adrenal (8X, 200K), Belladonna (200K), Beta Endorphin (6X, 200K), Citric Acid (30K), Coelliac Plexus (8X, 200K), Bryonia (200K), Interleukin-10 (8X, 200K), Mesenchyme (6X, 200K), Natrum Pyruvicum (30K), Pineal (2, 30K), Pituitary Gland (6X, 200K), Pyrogenium (200K), Transforming Growth Factor-1 (5C, 30K), Transforming Growth Factor-3 (5C, 30K)

Purpose:

Aconitum | Cell respiration
Anti-Interleukin-1 | Anti-inflammation
Apis | Anti-inflammation
Adrenal | Adrenal support
Belladonna | Drainage
Beta Endorphin | Pain relief
Citric Acid | Cell respiration
Coelliac Plexus | Neurological support
Bryonia | Drainage
Interleukin-10 | Anti-inflammation
Mesenchyme | Regeneration
Natrum Pyruvicum | Cell respiration
Pineal | Regeneration
Pituitary Gland | Regeneration
Pyrogenium | Drainage
Transforming Growth Factor-1 | Immune support
Transforming Growth Factor-3 | Regeneration

Uses

For the relief of inflammatory symptoms

Warnings

Stop use and ask a health care practitioner if symptoms persist for more than five days or worsen. If pregnant or breastfeeding, ask a health care practitioner before use.

Dosage

1-3 spray(s); 1-3 time(s) per day or as recommended by your health care practitioner.

KEEP OUT OF REACH OF CHILDREN

Keep this and all medicines out of reach of children.

Inactive ingredients

20% Alcohol and 80% Water

Other Information

Normal storage use.
Do not use if tamper-evident seal is broken or removed.

Questions

info@viatrexx.com

Principal Display Panel

ITEM: VPC0279
NDC 63776-249-14
Homeopathic remedy
Infla
• For the relief of inflammatory symptoms
Oral spray
30ml 1 oz
Viatrexx™ Bio Incorporated
Manufactured by Viatrexx
www.viatrexx.com
Newark, DE 19713

Infla
30 ml
1 oz
Viatrexx™ Bio Incorporated
ITEM: VPC0279
NDC: 63776-249-14
INDICATIONS:
For the relief of inflammatory symptoms
DIRECTIONS:
1-3 spray(s); 1-3 time(s) per day or as recommended by your health care practitioner.
Mfg. for
Viatrexx Bio Incorporated.
www.viatrexx.com
Newark, DE 19713